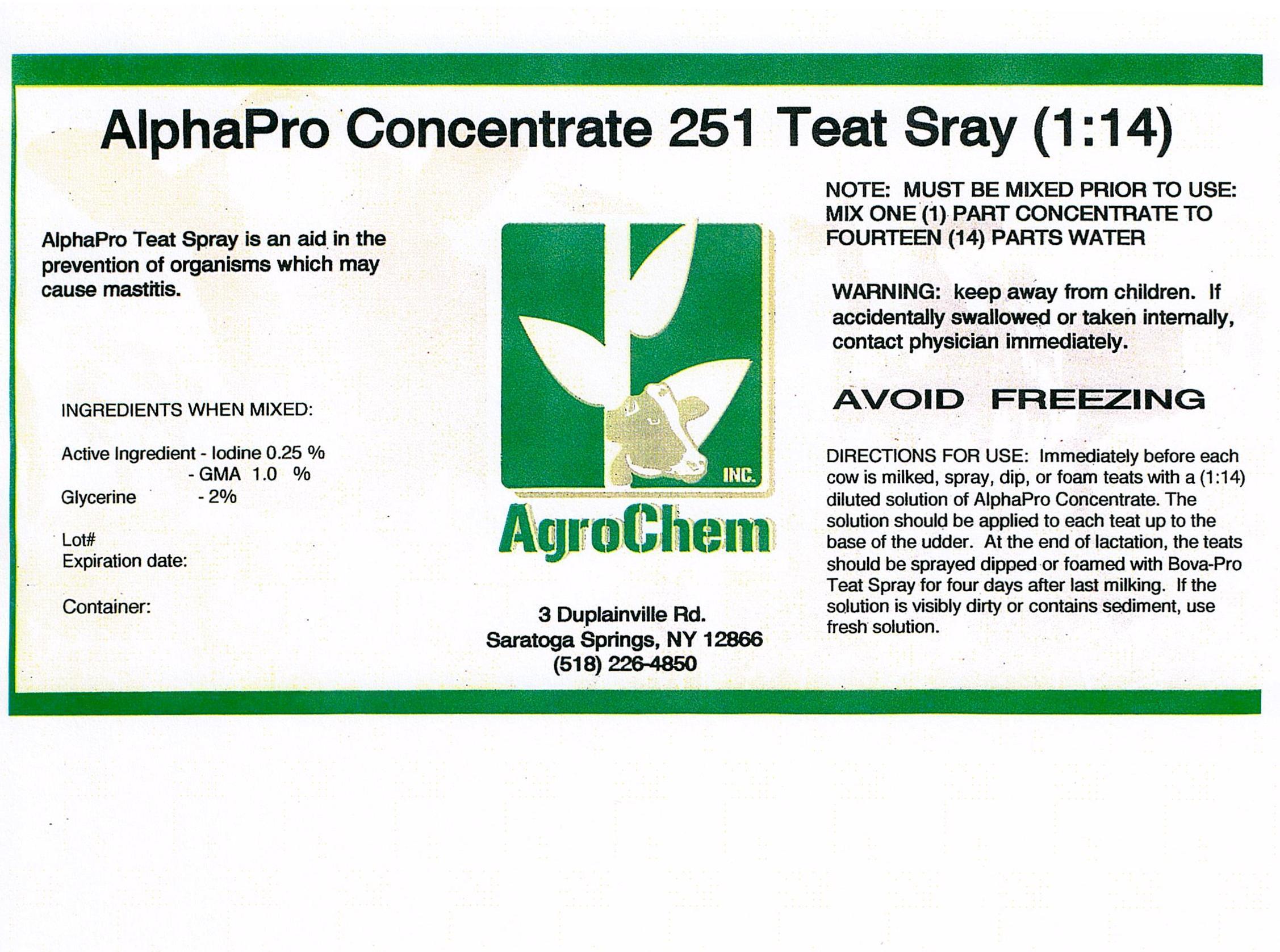 DRUG LABEL: Alpha Pro 251
NDC: 17307-2510 | Form: SOLUTION, CONCENTRATE
Manufacturer: AgroChem Inc.
Category: animal | Type: OTC ANIMAL DRUG LABEL
Date: 20130614

ACTIVE INGREDIENTS: IODINE .0025 kg/1 kg; LACTIC ACID .01 kg/1 kg
INACTIVE INGREDIENTS: WATER .94 kg/1 kg; GLYCERIN .019 kg/1 kg; SODIUM HYDROXIDE .004 kg/1 kg

Alpha Pro 251 Spray

Alpha Pro 251 Concentrate Spray description

AlphaPro Teat Spray is an aid in the

prevention of organisms which may

cause mastitis

Ingredients

INGREDIENTS WHEN MIXED;

Active ingredient – Iodine 0.25%

GMA 1.0%

Glycerine 2%

Warning

WARNING: Keep away from children. If

accidentally swallowed or taken internally,

contact physician immediately

Instructions for Use

NOTE: MUST BE MIXED PRIOR TO USE:

MIX ONE (1) PART CONCENTRATE TO

FOURTEEN (14) PARTS WATER

AVOID FREEZING

DIRECTIONS FOR USE: Immediately before each

Cow is milked, spray, dip or foam teats with a (1:14)

diluted solution of AlphaPro Concentrate. The

solution should be applied to each teat up to the

base of the udder. At the end of lactation, the teats

should be sprayed dipped or foamed with Bova-Pro

teat Spray for four days after last milking. If the

solution is visibly dirty or contains sediment, use

fresh solution.

AlphaPro Concentrate 251 Teat Spray

Place holder text